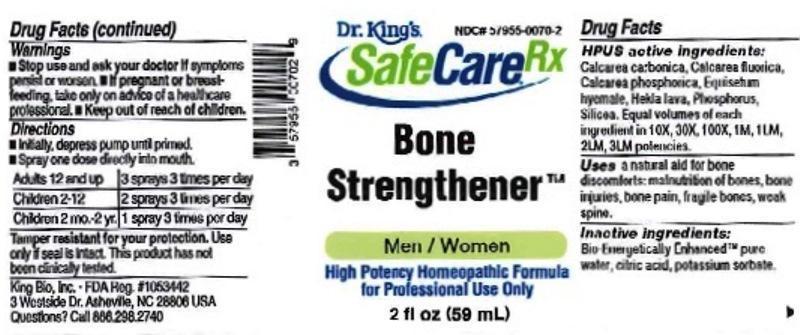 DRUG LABEL: Bone Strengthener
NDC: 57955-0070 | Form: LIQUID
Manufacturer: King Bio Inc.
Category: homeopathic | Type: HUMAN OTC DRUG LABEL
Date: 20170213

ACTIVE INGREDIENTS: OYSTER SHELL CALCIUM CARBONATE, CRUDE 10 [hp_X]/59 mL; CALCIUM FLUORIDE 10 [hp_X]/59 mL; TRIBASIC CALCIUM PHOSPHATE 10 [hp_X]/59 mL; EQUISETUM HYEMALE 10 [hp_X]/59 mL; HEKLA LAVA 10 [hp_X]/59 mL; PHOSPHORUS 10 [hp_X]/59 mL; SILICON DIOXIDE 10 [hp_X]/59 mL
INACTIVE INGREDIENTS: WATER; ANHYDROUS CITRIC ACID; POTASSIUM SORBATE

Bone Strengthener™

ACTIVE INGREDIENT

Drug Facts__________________________________________________________________________________________________________

HPUS active ingredients: Calcarea carbonica, Calcarea fluorica, Calcarea phosphorica, Equisetum hyemale, Hekla lava, Phosphorus, Silicea. Equal volumes of each ingredient in 10X, 30X, 100X,1M, 1LM, 2LM, 3LM potencies.

INDICATIONS AND USAGE

Uses a natural aid for bone discomforts: malnutrition of bones, bone injuries, bone pain, fragile bones, weak spine.

Inactive Ingredients:

Bio-Energetically Enhanced™ pure water, citric acid and potassium sorbate.

Warnings

- Stop use and ask your doctor if symptoms persist or worsen.
- If pregnant or breast-feeding, take only on advice of a healthcare professional.

- Keep out of reach of children.

Directions

- Initially, depress pump until primed.
- Spray one dose directly into mouth.
- Adults 12 and up: 3 sprays 3 times per day.
- Children 2-12 years: 2 sprays 3 times per day.
- Children 2 mo-2 yr: 1 spray 3 times per day.

OTHER SAFETY INFORMATION

Tamper resistant for your protection. Use only if seal is intact. This product has not been independently tested.

PURPOSE

Uses a natural aid for bone discomforts:

- malnutrition of bones
- bone injuries
- bone pain
- fragile bones
- weak spine